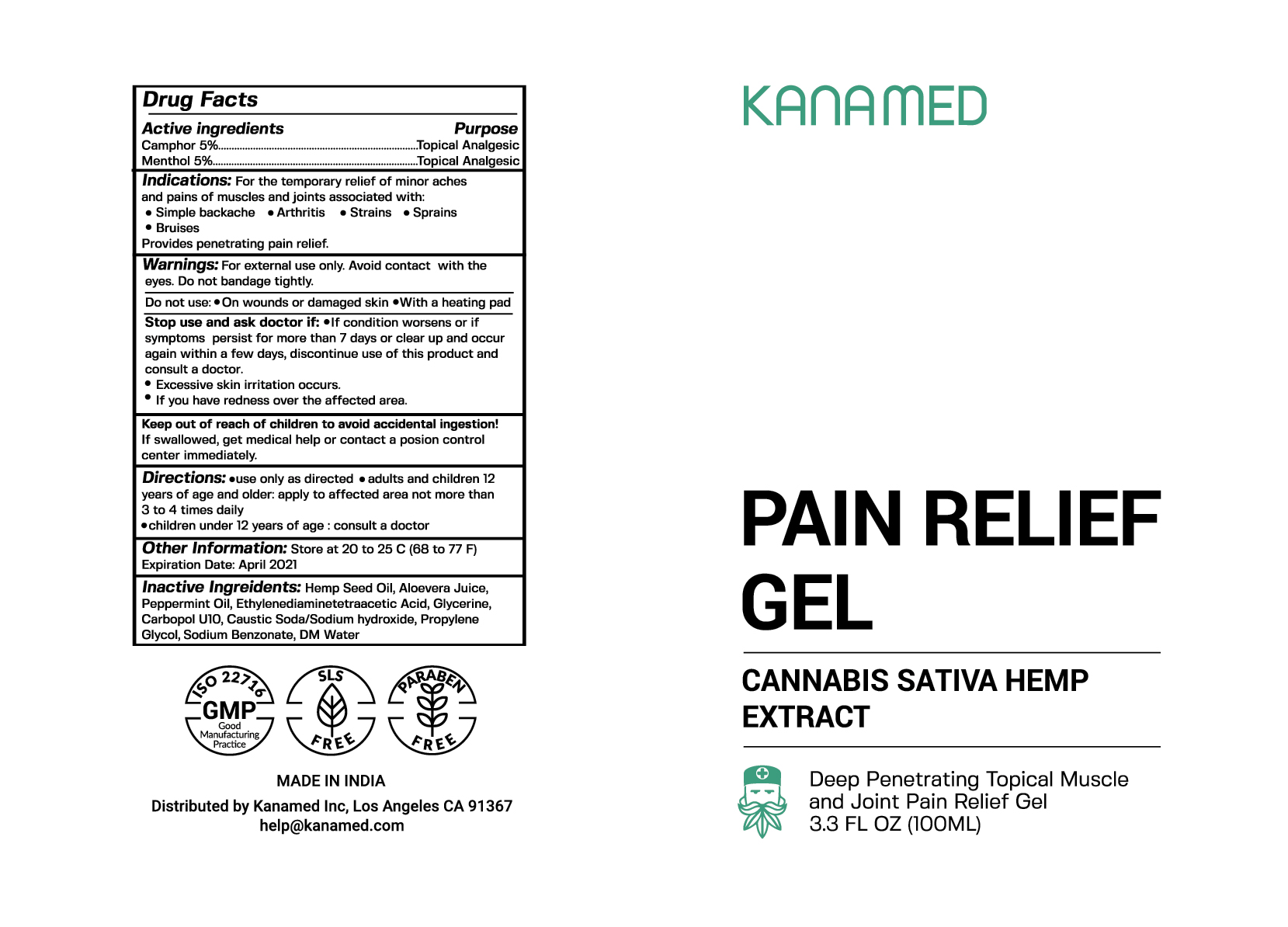 DRUG LABEL: Pain Relief Gel
NDC: 73239-1904 | Form: GEL
Manufacturer: Kanamed Inc.
Category: otc | Type: HUMAN OTC DRUG LABEL
Date: 20191024

ACTIVE INGREDIENTS: MENTHOL 5 mg/100 mL; CAMPHOR (NATURAL) 5 mg/100 mL
INACTIVE INGREDIENTS: ALOE VERA WHOLE; HEMP; WATER 1 mg/100 mL

Pain Relief Gel

ACTIVE INGREDIENT

Menthol 5% Topical Analgesic

Camphor 5% Topical Analgesic

INDICATIONS AND USAGE

temporarily relieves minor aches and pains of muscles and joints associated with

- arthritis
- simple backache
- muscle strains
- bruises
- sprains

INACTIVE INGREDIENT

- Hemp seed oil
- Aloe vera Juice
- Peppermint Oil
- Ethylenediaminetetraacetic Acid
- Glycerine
- Carbopol U10
- Caustic Soda/Sodium hydroxide
- Propylene Glycol
- Sodium Benzonate
- DM Water

DOSAGE AND ADMINISTRATION

Use only as directed
Adults and children 12 years of age and older apply to affected area not more than 3 to 4 times daily
Children under the age of 12 years of age consult a doctor

WARNINGS

- For external use only
- Only use as directed
- Do not allow contact with eyes
- Do not bandage tightly

STOP use and ask a doctor if:

- symptoms last more than 7 days or clear up and occur again within a few days
- Excessive skin irritation occurs
- If you have redness over the affected area

Keep out of reach of children.

PURPOSE

Topical Analgesic

OTHER SAFETY INFORMATION

Store at room temperature